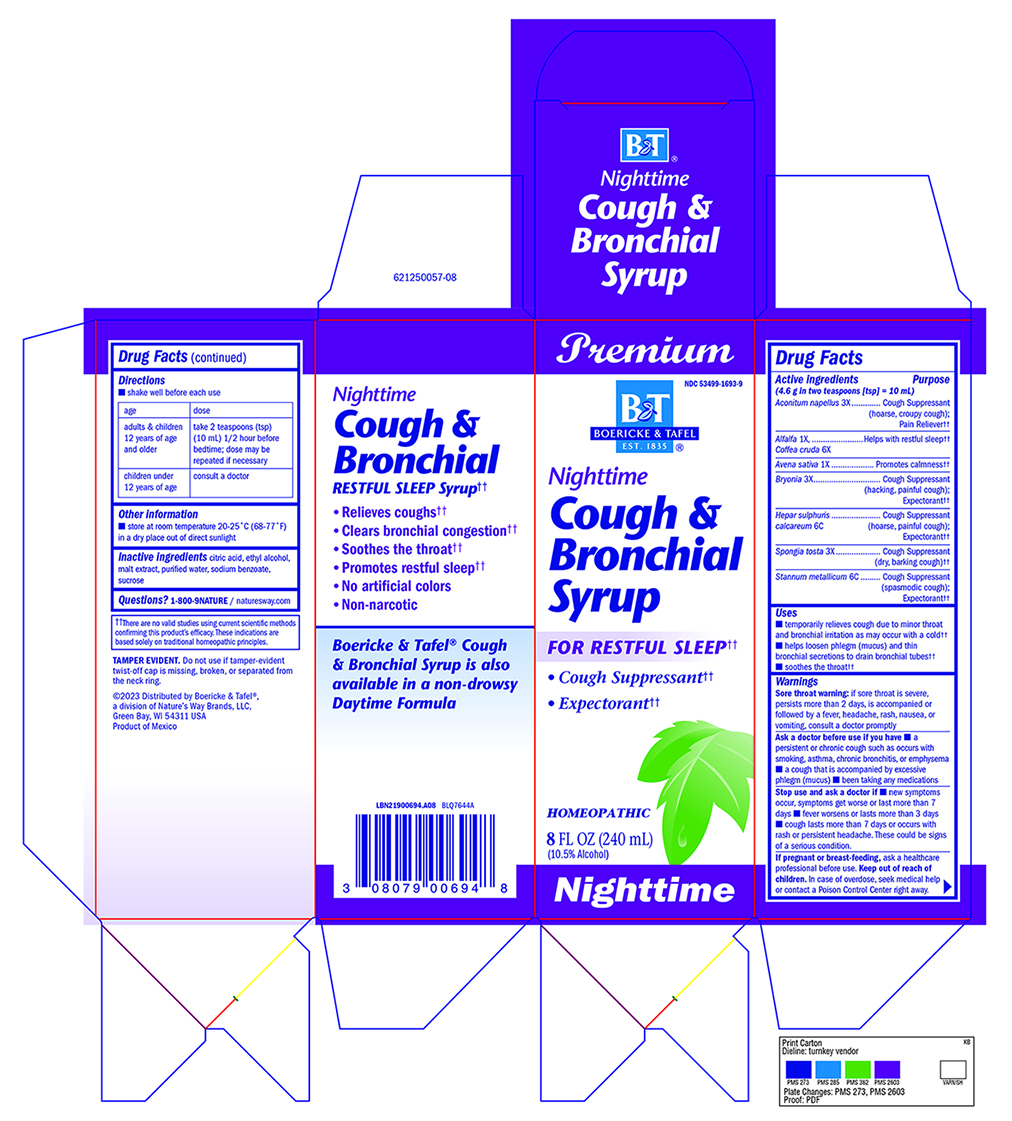 DRUG LABEL: Cough and Bronchial Nighttime Syrup
NDC: 68466-1009 | Form: SYRUP
Manufacturer: Schwabe Mexico S.A. DE C.V.
Category: homeopathic | Type: HUMAN OTC DRUG LABEL
Date: 20251204

ACTIVE INGREDIENTS: ACONITUM NAPELLUS 3 [hp_X]/120 mL; BRYONIA ALBA ROOT 3 [hp_X]/120 mL; CALCIUM SULFIDE 6 [hp_C]/120 mL; SPONGIA OFFICINALIS SKELETON, ROASTED 3 [hp_X]/120 mL; TIN 6 [hp_C]/120 mL; MEDICAGO SATIVA LEAF 1 [hp_X]/120 mL; OAT 1 [hp_X]/120 mL; ARABICA COFFEE BEAN 6 [hp_X]/120 mL
INACTIVE INGREDIENTS: ALCOHOL; ANHYDROUS CITRIC ACID; BARLEY MALT; WATER; SODIUM BENZOATE; SUCROSE

Cough and Bronchial Nighttime Syrup

Active Ingredient

Acontinum napellus 3X

Alfalfa 1X

Coffea cruda 6X

Avena sativa 1X

Bryonia 3X

Hepar sulphuris calcareum 6C

Spongia tosta 3X

Stannum metallicum 6C

Inactive Ingredient

citric acid

ethyl alcohol

malt extract

purified water

sodium benzoate

sucrose

Dosage & Administration

Directions

Shake well before each use.

Adults & children 12 years of age and older: Take 2 teaspoons (tsp) (10mL) 1/2 hour before bedtime. Dose may be repeated if necessary.

Children under 12 years of age: Consult a doctor.

Indications & Usage

Temporarily relieves coughs due to minor throat and bronchial irritation as may occur with a cold.

Helps loosen phlegm (mucus) and thin bronchial secretions to drain bronchial tubes.

Soothes the throat.

Purpose

Temporarily relieves coughs due to minor throat and bronchial irritation as may occur with a cold.

Helps loosen phlegm (mucus) and thin bronchial secretions to drain bronchial tubes.

Soothes the throat.

Warnings

Sore Throat Warning: if sore throat is severe, persists more than 2 days, is accompanied or followed by a fever, headache, rash, nausea, or vomiting, consult a doctor promptly.

Ask a doctor before use if you have a persistent or chronic cough such as occurs with smoking, asthma, chronic bronchitis, or emphysema, a cough that is accompanied by excessive phlegm (mucus), been taking any medications.

Stop use

Stop use and ask a doctor if new symptoms occur, symptoms get worse or last more than 7 days, fever worsens or lasts more than 3 days, cough last more than 7 days or occurs with rash or persistent headache.

These could be signs of a serious condition.

Pregnancy or breast feeding

If pregnant or breast-feeding, ask a healthcare professional before use.

Keep out of the reach of children

Overdose

In case of overdose, seek medical help or contact a Poison Control Center right away.